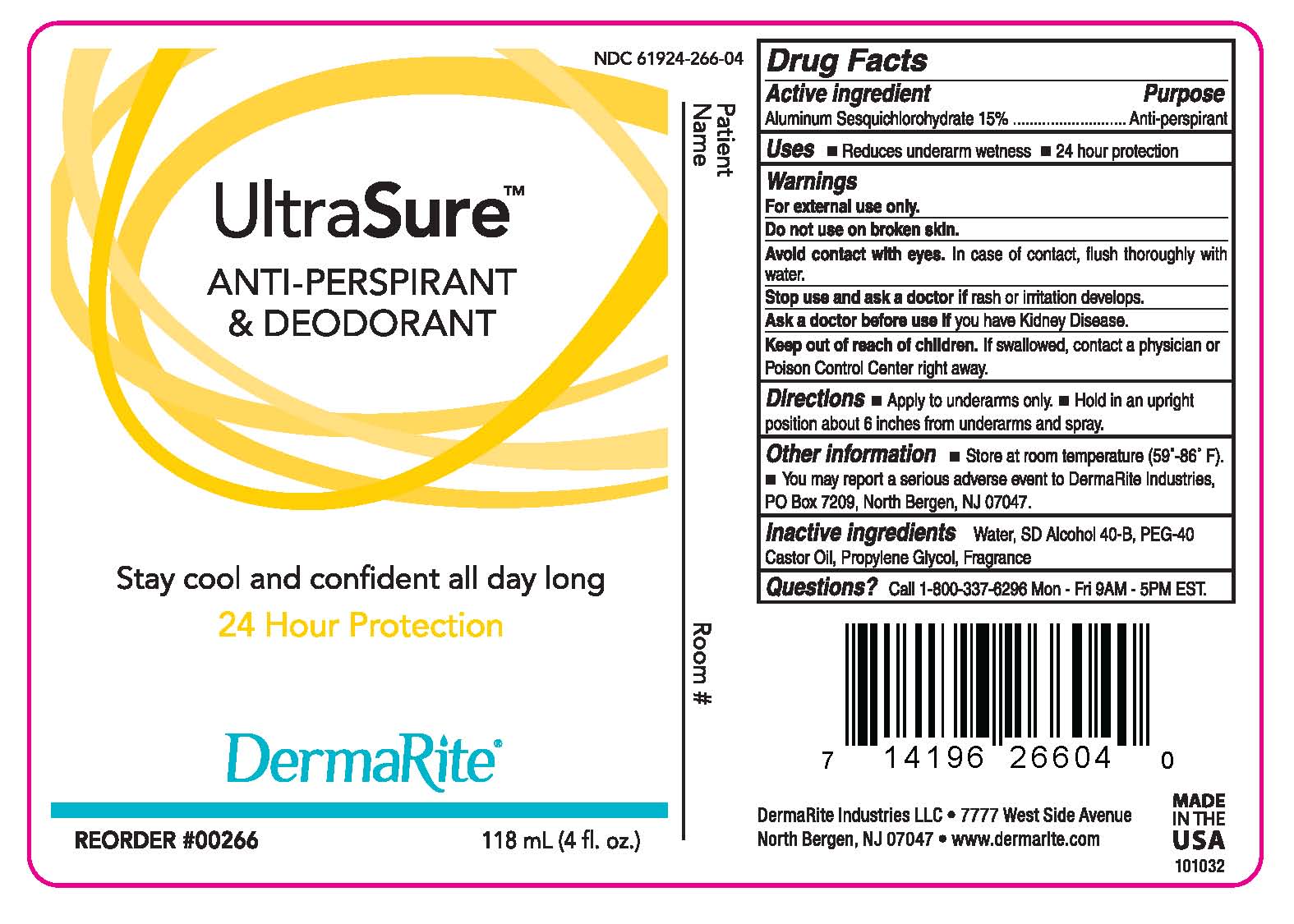 DRUG LABEL: UTRASURE
NDC: 61924-266 | Form: SPRAY
Manufacturer: DermaRite  Industries LLC
Category: otc | Type: HUMAN OTC DRUG LABEL
Date: 20241205

ACTIVE INGREDIENTS: ALUMINUM SESQUICHLOROHYDRATE 0.15 g/100 mL
INACTIVE INGREDIENTS: PEG-40 CASTOR OIL; PROPYLENE GLYCOL; ALCOHOL; WATER

DRUG LISTING:ULTRASURE SPRAY

Active Ingredient

Aluminum Sesquichlorohydrate 15%

Purpose:

Anti-perspirant

Uses:

- Reduce underarm wetness
- 24 hour protection

Warnings:

- For external use only.
- Do not use on broken skin.
- Avoid contact with eyes. In case of contact, flush thoroughly with water.
- Stop use and ask doctor if you have Kidney Disease.

Warnings:

- Keep out of reach of children. If swallowed, contact physician or Poison Control Center right away.

Directions:

- Apply to under arms only.
- Hold in an upright position about 6 inches from the underarm and spray.

Other Information

- Store at room temperature (59°-86°F).
- You may report a serious adverse event to DermaRite Industries, PO Box 7209, North Bergen, NJ 07047

Inactive Ingredients:

Fragrance, PEG-40 Castor Oil, Propylene Glycol, SD Alcohol 40-B, Water

Questions?

Call 1-800-337-6296 Mon-Fri 9AM-5PM EST.